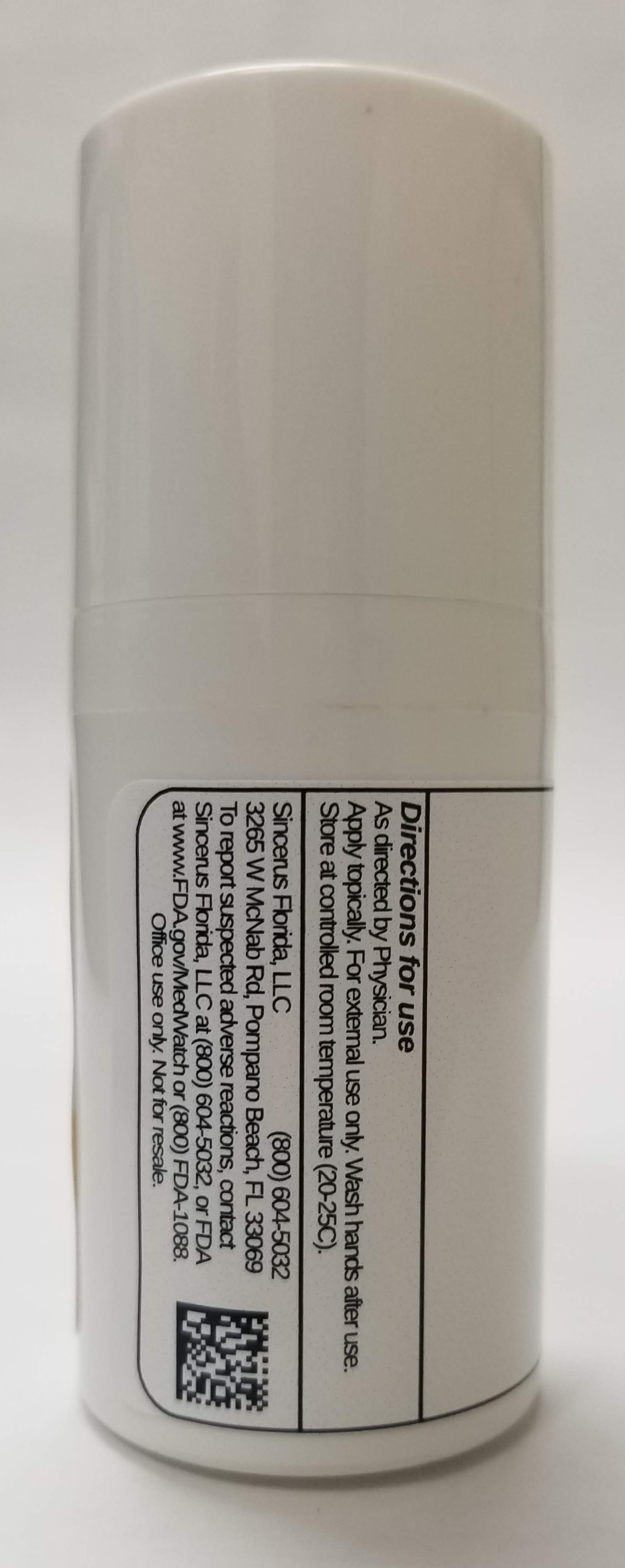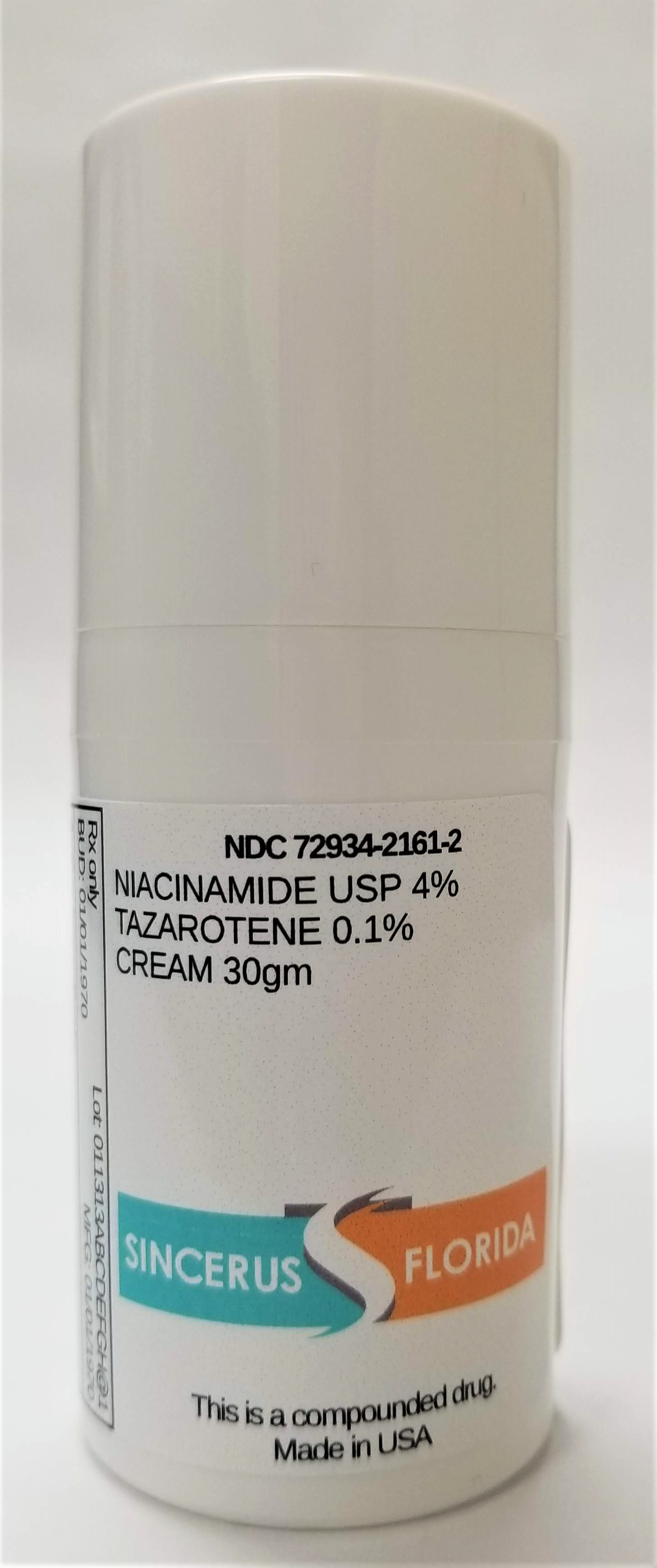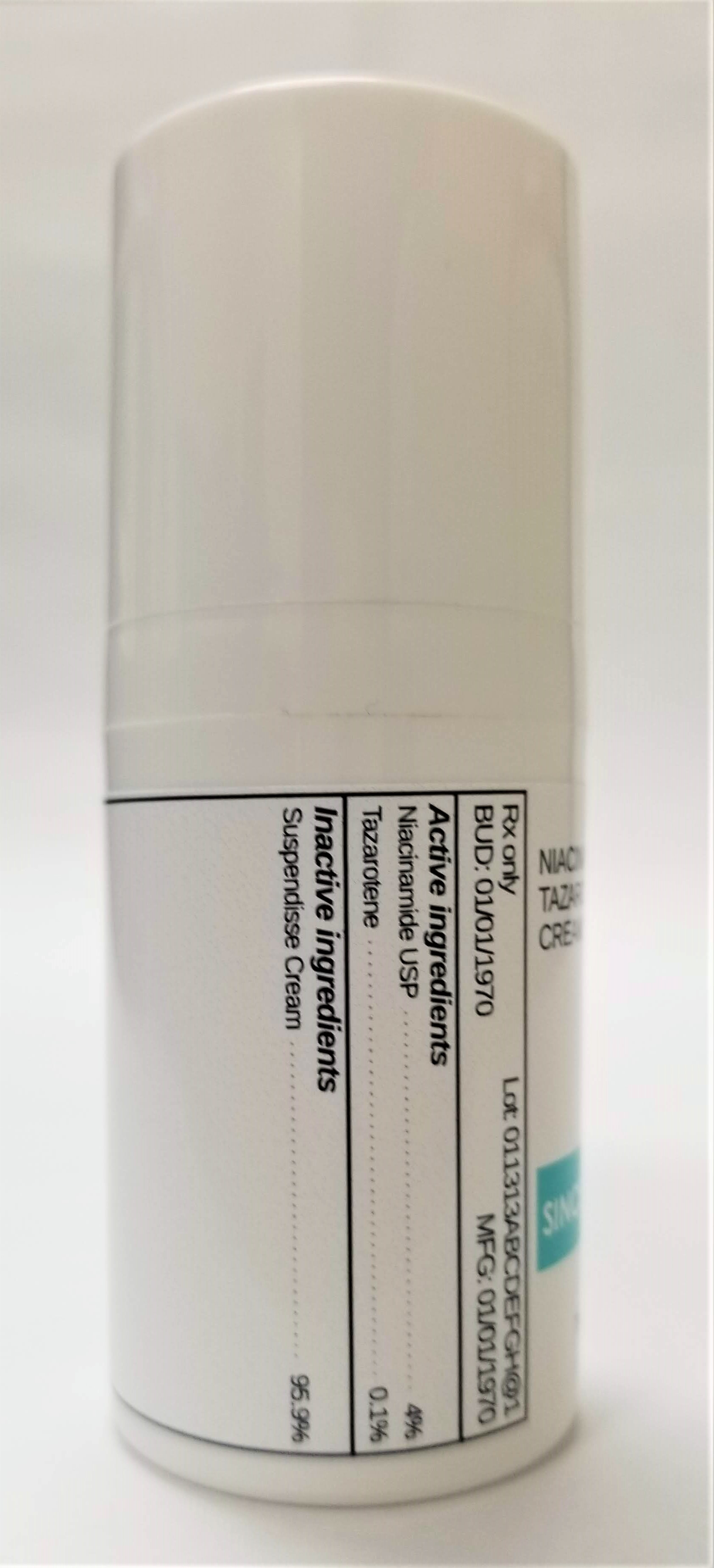 DRUG LABEL: NIACINAMIDE 4% / TAZAROTENE 0.1%
NDC: 72934-2161 | Form: CREAM
Manufacturer: Sincerus Florida, LLC
Category: prescription | Type: HUMAN PRESCRIPTION DRUG LABEL
Date: 20190423

ACTIVE INGREDIENTS: TAZAROTENE 0.1 g/100 g; NIACINAMIDE 4 g/100 g

NIACINAMIDE 4% / TAZAROTENE 0.1%